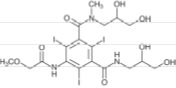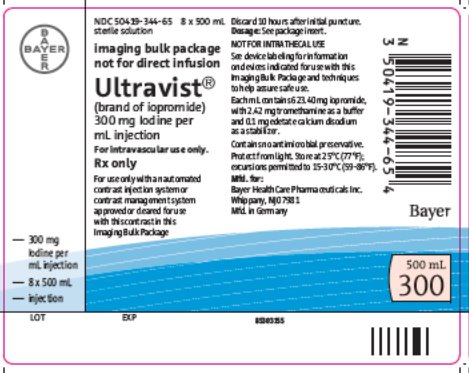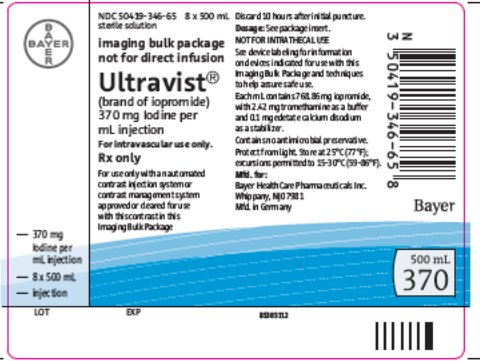 DRUG LABEL: Ultravist
NDC: 50419-344 | Form: INJECTION
Manufacturer: Bayer HealthCare Pharmaceuticals Inc.
Category: prescription | Type: HUMAN PRESCRIPTION DRUG LABEL
Date: 20230425

ACTIVE INGREDIENTS: IOPROMIDE 300 mg/1 mL
INACTIVE INGREDIENTS: EDETATE CALCIUM DISODIUM; TROMETHAMINE; SODIUM HYDROXIDE; HYDROCHLORIC ACID

HIGHLIGHTS OF PRESCRIBING INFORMATION

These highlights do not include all the information needed to use ULTRAVIST IMAGING BULK PACKAGE safely and effectively. See full prescribing information for ULTRAVIST IMAGING BULK PACKAGE.
ULTRAVIST (iopromide) injection, for intravenous use
Initial U.S. Approval: 1995

RECENT MAJOR CHANGES

Warnings and Precautions, Thyroid Dysfunction in Pediatric Patients 0 to 3 Years of Age (5.6) 4/2023

WARNING: NOT FOR INTRATHECAL USE

See full prescribing information for complete boxed warning.

Inadvertent intrathecal administration may cause death, convulsions, cerebral hemorrhage, coma, paralysis, arachnoiditis, acute renal failure, cardiac arrest, seizures, rhabdomyolysis, hyperthermia, and brain edema.

1 INDICATIONS AND USAGE

ULTRAVIST Imaging Bulk Package is a radiographic contrast agent indicated for contrast computed tomography (CT) imaging of head and body (300 mg Iodine per mL and 370 mg Iodine per mL) (1)

For use only with an automated contrast injection system, contrast management system, or contrast media transfer set approved or cleared for use with this contrast agent in this Imaging Bulk Package.

2 DOSAGE AND ADMINISTRATION

- Individualize the volume and concentration of ULTRAVIST injection to be used for a vascular procedure, according to the specific dosing tables. Adjust the dose accounting for factors such as age, body weight, size of the vessel and the rate of blood flow within the vessel. (2.1, 2.2, 2.3)
- For Intravenous use, only (2.4)
- Not for direct infusion (2.4)

3 DOSAGE FORMS AND STRENGTHS

ULTRAVIST injection IMAGING Bulk Package is available in two strengths: 300 mg Iodine per mL and 370 mg Iodine per mL. (3)

4 CONTRAINDICATIONS

- ULTRAVIST injection is contraindicated for intrathecal use. (4)
- Preparatory dehydration (for example, prolonged fasting and the administration of a laxative before ULTRAVIST injection) is contraindicated in pediatric patients because of risk of renal failure. (4)

5 WARNINGS AND PRECAUTIONS

- Anaphylactoid Reactions: Life-threatening or fatal anaphylactoid reactions may occur during or after ULTRAVIST injection administration, particularly in patients with allergic disorders. (5.1)
- Contrast Induced Acute Kidney Injury: Acute renal failure may occur following ULTRAVIST injection administration, particularly in patients with renal insufficiency, diabetes, multiple myeloma. Exercise caution and use the lowest necessary dose of ULTRAVIST injection in patients with renal dysfunction. (5.2)
- Cardiovascular Reactions: Hemodynamic disturbances including shock and cardiac arrest may occur during or shortly after administration of ULTRAVIST injection.(5.3)
- Thromboembolic Complications: Angiography may be associated with local and distal organ damage, ischemia, thromboembolism and organ failure. In angiographic procedures, consider the possibility of dislodging plaques or damaging or perforating the vessel wall. The physicochemical properties of the contrast agent, the dose and the speed of injection can influence the reactions. (5.4)
- Thyroid Dysfunction in Pediatric Patients 0 to 3 Years of Age: Individualize thyroid function monitoring based on risk factors such as prematurity (5.6)

6 ADVERSE REACTIONS

Most common adverse reactions (>1%) are headache, nausea, injection site and infusion site reactions, vasodilatation, vomiting, back pain, urinary urgency, chest pain, pain, dysgeusia and abnormal vision. (6)

To report SUSPECTED ADVERSE REACTIONS, contact Bayer HealthCare Pharmaceuticals Inc. at 1-888-842-2937 or FDA at 1-800-FDA-1088 or www.fda.gov/medwatch.

8 USE IN SPECIFIC POPULATIONS

- Lactation: Advise lactating women that interruption of breast feeding is not necessary, however, a lactating woman may consider interrupting breastfeeding and pumping and discarding breast milk for 12 to 24 hours after ULTRAVIST Injection administration to minimize exposure to the breastfed infant (8.2)
- The safety and efficacy of ULTRAVIST injection has been established in the pediatric population over 2 years of age. (8.4)

FULL PRESCRIBING INFORMATION

WARNING: NOT FOR INTRATHECAL USE

Inadvertent intrathecal administration may cause death, convulsions, cerebral hemorrhage, coma, paralysis, arachnoiditis, acute renal failure, cardiac arrest, seizures, rhabdomyolysis, hyperthermia, and brain edema. [See Contraindications (4).]

1 INDICATIONS AND USAGE

ULTRAVIST® injection is an iodinated contrast agent indicated In

Adults

- For Computed Tomography (CT) of the head and body (intrathoracic, intra-abdominal and retroperitoneal regions) for the evaluation of neoplastic and non-neoplastic lesions in adults.
- The usefulness of contrast enhancement for the investigation of the retrobulbar space and of low grade or infiltrative glioma has not been demonstrated.

Pediatric Patients

- For Computed Tomography (CT) of the head and body

For use only with an automated contrast injection system, contrast management system, or contrast media transfer set approved or cleared for use with this contrast agent in this Imaging Bulk Package.

2 DOSAGE AND ADMINISTRATION

2.1 Important Administration Instructions

- ULTRAVIST IMAGING BULK PACKAGE is for intravenous use only not for direct infusion.
- Visually inspect ULTRAVIST injection for particulate matter and/or discoloration, whenever solution and container permit. Do not administer ULTRAVIST injection if particulate matter (including crystals) and/or discoloration is observed or if containers are defective. As ULTRAVIST injection is a highly concentrated solution, crystallization (milky-cloudy appearance and/or sediment at bottom, or floating crystals) may occur.
- Use sterile technique for all handling and administration of ULTRAVIST.
- Determine the volume and concentration of ULTRAVIST injection to be used considering factors such as age, body weight, size of the vessel and the rate of blood flow within the vessel; consider also extent of opacification required, structure(s) or area to be examined, disease processes affecting the patient, and equipment and technique to be employed. Specific dose adjustments for age, gender, weight and renal function have not been studied for ULTRAVIST injection. As with all iodinated contrast agents, lower doses may have less risk. The efficacy of ULTRAVIST injection below doses recommended has not been established.
- Administer ULTRAVIST at or close to body temperature.

Do not mix or inject ULTRAVIST injection in intravenous administration lines containing other drugs or total nutritional admixtures. ULTRAVIST can be mixed with saline when used in a power injector suitable for simultaneous injection of contrast and saline [see Dosage and Administration (2.2)].

- The maximum recommended total dose of iodine in adults is 86 grams; a maximum recommended total dose of iodine has not been established for pediatric patients.
- Hydrate patients, as appropriate, prior to and following the administration of ULTRAVIST injection [see Warnings and Precautions (5.2)].

2.2 Intravenous Procedures

- Computed Tomography (CT) (300 mg Iodine per mL and 370 mg Iodine per mL): see Table 1.

Table 1: Suggested ULTRAVIST injection Dosing for Adult Intravenous Contrast Administration
 | Contrast Computed Tomography; (300 mg Iodine per mL) | Contrast Computed Tomography; (370 mg Iodine per mL)
Head | 50 ml to 200 mL | 41 ml to 162 mL
Body; Single Contrast Phase
Bolus Injection | 50 ml to 200 mL | 41 ml to 162 mL
Rapid Infusion | 100 ml to 200 mL | 81 ml to 162 mL
Body; Multiple Phase Contrast | 50 ml to 200 mL total volume; Phase 1: 100% contrast; Phase 2: 20-60% contrast,; using a power injector suitable for simultaneous injection of contrast and saline | 41 ml to 162 mL total volume; Phase 1: 100% contrast,; Phase 2: 20-60% contrast,; using a power injector suitable for simultaneous injection of contrast and saline
Maximum Total Dose | 200 mL (60 g iodine) | 162 mL (60 g iodine)

2.3 Pediatric Dosing

The recommended dose in children over 2 years of age for Computerized Tomography of the head and body (300 mg Iodine per mL):

- 1 to 2 milliliters per kilogram (mL/kg) injected intravenously.
- [see Use in Specific Populations (8.4) and Clinical Pharmacology (12.3)].

Do not exceed the adult dose (200 mL)

2.4 Imaging Bulk Package Preparation Instructions

ULTRAVIST Imaging Bulk Package is for use only with an automated contrast injection system, contrast management system, or contrast media transfer set approved or cleared for use with this contrast agent in this Imaging Bulk Package. Please see drug and device labeling for information on devices indicated for use with this Imaging Bulk Package and techniques to help assure safe use.

1. The ULTRAVIST Imaging Bulk Package is to be used only in a room designated for radiological procedures that involve intravascular administration of a contrast agent.
2. Utilize aseptic technique for penetrating the container closure of the ULTRAVIST Imaging Bulk Package and transferring ULTRAVIST injection. The container closure may be penetrated only one time with a suitable sterile component of the automated contrast injection system, contrast management system, or contrast media transfer set approved or cleared for use with this contrast agent in this this Imaging Bulk Package.
3. Once the ULTRAVIST Imaging Bulk Package is punctured, do not be remove it from the work area during the entire period of use. Maintain the bottle in an inverted position such that container contents are in continuous contact with the dispensing set.
4. A maximum use time of 10 hours from initial puncture is permitted to complete fluid transfer. Discard any unused ULTRAVIST injection 10 hours after initial puncture of the Imaging Bulk Package.
5. After the container closure is punctured, if the integrity of the Imaging Bulk Package and the delivery system cannot be assured through direct continuous supervision, the Imaging Bulk Package and all associated disposables for the automated contrast injection system, contrast management system, or contrast media transfer set should be discarded.
Storage temperature of Imaging Bulk Package after the closure has been entered should not exceed 25°C (77°F) excursions permitted to 15–30°C (59–86°F); however, it is desirable that the contents be warmed to body temperature prior to injection.

3 DOSAGE FORMS AND STRENGTHS

ULTRAVIST injection is a nonionic, sterile, clear, colorless to slightly yellow, odorless, pyrogen-free aqueous solution of iopromide available as an Imaging Bulk Package in two strengths:

300 mg Iodine per mL provides 623.4 mg/mL iopromide

370 mg Iodine per mL provides 768.86 mg/mL iopromide

4 CONTRAINDICATIONS

- Do not administer ULTRAVIST injection intrathecally. Inadvertent intrathecal administration may cause death, convulsions, cerebral hemorrhage, coma, paralysis, arachnoiditis, acute renal failure, cardiac arrest, seizures, rhabdomyolysis, hyperthermia, and brain edema.
- Preparatory dehydration (for example, prolonged fasting and the administration of a laxative) before ULTRAVIST injection is contraindicated in pediatric patients because of risk of acute renal failure.

5 WARNINGS AND PRECAUTIONS

5.1 Hypersensitivity Reactions

Life-threatening or fatal, hypersensitivity reactions, may occur during or after ULTRAVIST injection administration. Manifestations include respiratory arrest, laryngospasm, bronchospasm, angioedema, and shock. Increased risk is associated with a history of previous reaction to a contrast agent (3-fold), a known sensitivity to iodine and known allergic disorders (that is, bronchial asthma, hay fever and food allergies) or other hypersensitivities (2-fold).

Monitor all patients for hypersensitivity reactions. Emergency facilities and personnel trained in the treatment of hypersensitivity reactions should be available for at least 30 to 60 minutes after ULTRAVIST injection administration.

5.2 Contrast Induced Acute Kidney Injury

Acute kidney injury, including renal failure, may occur after intravascular administration of ULTRAVIST injection. Risk factors include: pre-existing renal insufficiency, dehydration, diabetes mellitus, congestive heart failure, advanced vascular disease, elderly age, concomitant use of nephrotoxic or diuretic medications, multiple myeloma / paraproteinemia, repetitive and/or large doses of ULTRAVIST injection.

Use the lowest necessary dose of ULTRAVIST injection in patients with renal impairment. Hydrate patients, as appropriate, prior to and following ULTRAVIST injection administration.

5.3 Cardiovascular Reactions

ULTRAVIST injection increases the circulatory osmotic load and may induce acute or delayed hemodynamic disturbances in patients with congestive heart failure, severely impaired renal function, combined renal and hepatic disease, combined renal and cardiac disease, particularly when repetitive and/or large doses are administered [see Drug Interactions (7)].

Among patients who have had cardiovascular reactions, most deaths occurred from the start of injection to 10 minutes later; the main feature was cardiac arrest with cardiovascular disease as the main underlying factor. Reports of hypotensive collapse and shock have been published.

The administration of ULTRAVIST injection may cause pulmonary edema in patients with heart failure. Based upon published reports, deaths from the administration of iodinated contrast agents range from 6.6 per 1 million (0.00066 percent) to 1 in 10,000 patients (0.01 percent). Observe patients with preexisting cardiovascular disease for several hours following ULTRAVIST injection administration.

5.4 Thromboembolic Complications

- Angiography may be associated with local and distal organ damage, ischemia, thromboembolism and organ failure including stroke, brachial plexus palsy, chest pain, myocardial infarction, sinus arrest, hepato-renal function abnormalities. For these reasons, meticulous angiographic techniques are recommended, including close attention to guide wire and catheter manipulation, use of manifold systems and/or three-way stopcocks, frequent catheter flushing with heparinized saline solutions and minimizing the length of the procedure. In angiographic procedures, consider the possibility of dislodging plaques or damaging or perforating the vessel wall with resultant pseudoaneurysms, hemorrhage at puncture site, dissection of coronary artery during catheter manipulations and contrast agent injection. The physicochemical properties of the contrast agent, the dose and the speed of injection can influence the reactions. Test injections to ensure proper catheter placement are suggested. Increased thrombosis and activation of the complement system has also occurred. Specialized personnel, and adequate equipment and facilities for immediate resuscitation and cardioversion are necessary. Monitor electrocardiograms and vital signs throughout the procedure.
- Exercise care when performing venography in patients with suspected thrombosis, phlebitis, severe ischemic disease, local infection, venous thrombosis or a totally obstructed venous system.
- Clotting may occur when blood remains in contact with syringes containing iodinated contrast agents.
  Avoid angiography whenever possible in patients with homocystinuria because of the risk of inducing thrombosis and embolism [see Clinical Pharmacology (12.2)].

5.5 Reactions in Patients with Hyperthyroidism, Pheochromocytoma, or Sickle Cell Disease

Thyroid storm in patients with hyperthyroidism. Thyroid storm has occurred after the intravascular use of iodinated contrast agents in patients with hyperthyroidism, or with an autonomously functioning thyroid nodule. Evaluate the risk in such patients before use of any iodinated contrast agent.

Hypertensive crises in patients with pheochromocytoma. Administer iodinated contrast agents with extreme caution in patients with known or suspected pheochromocytoma. Inject the minimum amount of contrast necessary. Assess the blood pressure throughout the procedure, and have measures for treatment of a hypertensive crisis readily available.

Sickle cell disease. Contrast agents may promote sickling in individuals who are homozygous for sickle cell disease when administered intravascularly.

5.6 Thyroid Dysfunction in Pediatric Patients 0 to 3 Years of Age

Thyroid dysfunction characterized by hypothyroidism or transient thyroid suppression has been reported after both single exposure and multiple exposures to iodinated contrast media (ICM) in pediatric patients 0 to 3 years of age.

Younger age, very low birth weight, prematurity, underlying medial conditions affecting thyroid function, admission to neonatal or pediatric intensive care units, and congenital cardiac conditions are associated with an increased risk of hypothyroidism after ICM exposure. Pediatric patients with congenital cardiac conditions may be at the greatest risk given that they often require high doses of contrast during invasive cardiac procedures.

An underactive thyroid during early life may be harmful for cognitive and neurological development and may require thyroid hormone replacement therapy. After exposure to ICM, individualize thyroid function monitoring based on underlying risk factors, especially in term and preterm neonates.

The safety and effectiveness of ULTRAVIST in pediatric patients younger than 2 years of age have not been established, and ULTRAVIST is not approved for use in pediatric patients younger than 2 years of age [see Use in Specific Populations (8.4)].

5.7 Extravasation

Extravasation of ULTRAVIST injection may cause tissue necrosis and/or compartment syndrome, particularly in patients with severe arterial or venous disease.

5.8 Increased Radiation Exposure

The decision to use contrast enhancement is associated with risk and increased radiation exposure. Use contrast after a careful evaluation of clinical, other radiologic data, and the results of non-contrast CT findings, taking into account the increased radiation dose and other risks.

5.9 Interference with Image Interpretation

As with other iodinated contrast agents, the use of ULTRAVIST injection may obscure some lesions which were seen on non-contrast CT scans. Calcified lesions are less likely to enhance. The enhancement of tumors after therapy may decrease. The opacification of the inferior vermis following contrast agent administration has resulted in false-positive diagnosis. Cerebral infarctions of recent onset may be better visualized with contrast enhancement. However, older infarctions may be obscured by the contrast agent.

In patients with normal blood-brain barriers and renal failure, iodinated contrast agents have been associated with blood-brain barrier disruption and accumulation of contrast in the brain. Accumulation of contrast in the brain also occurs in patients where the blood-brain barrier is known or suspected to be disrupted.

5.10 Severe Cutaneous Adverse Reactions

Severe cutaneous adverse reactions (SCAR) may develop from 1 hour to several weeks after intravascular contrast agent administration. These reactions include Stevens-Johnson syndrome and toxic epidermal necrolysis (SJS/TEN), acute generalized exanthematous pustulosis (AGEP) and drug reaction with eosinophilia and systemic symptoms (DRESS). Reaction severity may increase and time to onset may decrease with repeat administration of contrast agent; prophylactic medications may not prevent or mitigate severe cutaneous adverse reactions. Avoid administering ULTRAVIST to patients with a history of a severe cutaneous adverse reaction to ULTRAVIST.

6 ADVERSE REACTIONS

The most important adverse drug reactions in patients receiving ULTRAVIST are anaphylactoid shock, contrast induced acute kidney injury, coma, cerebral infarction, stroke, brain edema, convulsion, arrhythmia, cardiac arrest, myocardial ischemia, myocardial infarction, cardiac failure, bradycardia, cyanosis, hypotension, shock, dyspnea, pulmonary edema, respiratory insufficiency and aspiration.

6.1 Clinical Trials Experience

Because clinical trials are conducted under widely varying conditions, adverse reaction rates observed in the clinical trials of a drug cannot be directly compared to rates in the clinical trials of another drug and may not reflect or predict the rates observed in practice.

The following table of incidence of reactions is based upon controlled clinical trials in which ULTRAVIST injection was administered to 1142 patients. This listing includes all reported adverse reactions regardless of attribution.

Adverse reactions are listed by System Organ Class and in decreasing order of occurrence for rates greater than 1% in the ULTRAVIST injection group: see Table 2.

Table 2: Adverse Reactions Reported in > 1% of Patients Who Received ULTRAVIST injection in Clinical Trials
System Organ Class | Adverse Reaction | ULTRAVIST injection
System Organ Class | Adverse Reaction | N=1142 (%)
Nervous system disorders | Headache | 46 (4)
Nervous system disorders | Dysgeusia | 15 (1.3)
Eye disorders | Abnormal Vision | 12 (1.1)
Cardiac disorders | Chest pain | 18 (1.6)
Vascular disorders | Vasodilatation | 30 (2.6)
Gastrointestinal disorders | Nausea | 42 (3.7)
Gastrointestinal disorders | Vomiting | 22 (1.9)
Musculoskeletal and connective tissue disorders | Back pain | 22 (1.9)
Renal and urinary disorders | Urinary urgency | 21 (1.8)
General disorders and administration site conditions | Injection site and infusion site reactions (hemorrhage, hematoma, pain, edema, erythema, rash) | 41 (3.7)
General disorders and administration site conditions | Pain | 13 (1.4)

One or more adverse reactions were recorded in 273 of 1142 (24%) patients during the clinical trials, coincident with the administration of ULTRAVIST injection or within the defined duration of the study follow-up period (24–72 hours). ULTRAVIST injection is often associated with sensations of warmth and/or pain.

Serious, life-threatening and fatal reactions have been associated with the administration of iodine-containing contrast media, including ULTRAVIST injection. In clinical trials 7/1142 patients given ULTRAVIST injection died 5 days or later after drug administration. Also, 10/1142 patients given ULTRAVIST injection had serious adverse events.

The following adverse reactions were observed in ≤1% of the subjects receiving ULTRAVIST injection:

Cardiac disorders: atrioventricular block (complete), bradycardia, ventricular extrasystole

Gastrointestinal disorders: abdominal discomfort, abdominal pain, abdominal pain upper, constipation, diarrhea, dry mouth, dyspepsia, gastrointestinal disorder, gastrointestinal pain, salivation increased, stomach discomfort, rectal tenesmus

General disorders and administration site conditions: asthenia, chest discomfort, chills, excessive thirst, extravasation, feeling hot, hyperhidrosis, malaise, edema peripheral, pyrexia

Immune system disorders: asthma, face edema

Investigations: blood lactate dehydrogenase increased, blood urea increased, hemoglobin increased, white blood cell count increased

Musculoskeletal and connective tissue disorders: arthralgia, musculoskeletal pain, myasthenia, neck pain, pain in extremity

Nervous system disorders: agitation, confusion, convulsion, dizziness, hypertonia, hypesthesia, incoordination, neuropathy, somnolence, speech disorder, tremor, paresthesia, visual field defect

Psychiatric disorders: anxiety

Renal and urinary disorders: dysuria, renal pain, urinary retention

Respiratory, thoracic and mediastinal disorders: apnea, cough increased, dyspnea, hypoxia, pharyngeal edema, pharyngitis, pleural effusion, pulmonary hypertension, respiratory disorder, sore throat

Skin and subcutaneous tissue disorders: erythema, pruritus, rash, urticaria

Vascular disorders: coronary artery thrombosis, flushing, hypertension, hypotension, peripheral vascular disorder, syncope, vascular anomaly

6.2 Postmarketing Experience

The following adverse reactions have been identified during post approval use of ULTRAVIST injection. Because these reactions are reported voluntarily from a population of uncertain size, it is not always possible to reliably estimate their frequency or establish a causal relationship to drug exposure.

Adverse reactions reported in foreign postmarketing surveillance and other trials with the use of ULTRAVIST injection include:

Cardiac disorders: cardiac arrest, ventricular fibrillation, atrial fibrillation,tachycardia, palpitations, congestive heart failure, myocardial infarction, angina pectoris

Ear and labyrinth disorders: vertigo, tinnitus

Endocrine disorders: hyperthyroidism, thyrotoxic crisis, hypothyroidism

Eye disorders: mydriasis, lacrimation disorder

Gastrointestinal disorders: dysphagia, swelling of salivary glands

Immune system disorders: anaphylactoid reaction (including fatal cases), respiratory arrest, anaphylactoid shock, angioedema, laryngeal edema, laryngospasm, bronchospasm, hypersensitivity

Musculoskeletal and connective tissue disorders: compartment syndrome in case of extravasation

Nervous system disorders: cerebral ischemia/infarction, paralysis, paresis, transient cortical blindness, aphasia, coma, unconsciousness, amnesia, hypotonia, aggravation of myasthenia gravis symptoms

Renal and urinary disorders: renal failure, hematuria

Respiratory, thoracic and mediastinal disorders: pulmonary edema, acute respiratory distress syndrome, asthma

Skin and subcutaneous tissue disorders: Reactions range from mild (e.g. rash, erythema, pruritus, urticaria and skin discoloration) to severe [e.g. Stevens-Johnson Syndrome and toxic epidermal necrolysis (SJS/TEN), acute generalized exanthematous pustulosis (AGEP) and drug reaction with eosinophilia and systemic symptoms (DRESS)].

Vascular disorders: vasospasm

6.3 Pediatrics

The overall character, quality, and severity of adverse reactions in pediatric patients are generally similar to those reported in adult patients. Additional adverse reactions reported in pediatric patients from foreign marketing surveillance or other information are: epistaxis, angioedema, migraine, joint disorder (effusion), muscle cramps, mucous membrane disorder (mucosal swelling), conjunctivitis, hypoxia, fixed eruptions, vertigo, diabetes insipidus, and brain edema [see Use in Specific Populations (8.4)].

7 DRUG INTERACTIONS

7.1 Drug-Drug Interactions

In patients with renal impairment, biguanides can cause lactic acidosis. ULTRAVIST injection appears to increase the risk of biguanide induced lactic acidosis, possibly as a result of worsening renal function [see Warnings and Precautions (5.2)].

Patients on beta-blockers may be unresponsive to the usual doses of epinephrine used to treat allergic reactions. Because of the risk of hypersensitivity reactions, use caution when administering iodinated contrast agents to patients taking beta-blockers.

Interleukins are associated with an increased prevalence of delayed hypersensitivity reactions after iodinated contrast agent administration. These reactions include fever, chills, nausea, vomiting, pruritus, rash, diarrhea, hypotension, edema, and oliguria.

Renal toxicity has been reported in a few patients with liver dysfunction who were given an oral cholecystographic agent followed by intravascular contrast agents. Administration of any intravascular contrast agent should therefore be postponed in patients who have recently received a cholecystographic contrast agent.

Do not mix other drugs with ULTRAVIST injection except saline [see How Supplied/Storage and Handling (16)].

7.2 Drug-Laboratory Test Interactions

Thyroid Function Tests:

The results of protein bound iodine and radioactive iodine uptake studies, which depend on iodine estimation, will not accurately reflect thyroid function for at least 16 days following administration of iodinated contrast agents. However, thyroid function tests which do not depend on iodine estimations, for example, T3 resin uptake and total or free thyroxine (T4) assays are not affected.

Laboratory Assay of Coagulation Parameters, Fibrinolysis and Complement System:

The effect of iopromide on coagulation factors in in vitro assays increased with the administered dose. Coagulation, fibrinolysis and complement activation were evaluated with standard citrated human plasma in the following assays: thrombin time, thrombin coagulase time, calcium thromboplastin time, partial thromboplastin time, plasminogen, thrombin, alpha-2 antiplasmin and factor XIIa activity. Thrombin inhibition was almost complete. Data on reversibility are not available. The thrombin time increased from approximately 20 seconds at an iopromide concentration of 10 mg Iodine per mL, up to 100 seconds at an iopromide concentration of 70 mg Iodine per mL.

The PTT increased from approximately 50 seconds at an iopromide concentration of 10 mg Iodine per mL, up to approximately 100 seconds at an iopromide concentration of 70 mg Iodine per mL. A similar increase was noted in the thrombin coagulase time. Lesser effects were noted in the calcium thromboplastin time. Coagulation time increased from 13.5 to 23 seconds at the highest iopromide concentration of 70 mg Iodine per mL. The Hageman factor split products decreased by about 20% over the range of 10 to 70 mg Iodine per mL of iopromide. Plasminogen was relatively stable. There was no evidence of activation of fibrinolysis. The complement alternate pathway was activated. Factor B conversion increased in a dose dependent manner. The duration of these effects was not studied.

In vitro studies with human blood showed that iopromide had a slight effect on coagulation and fibrinolysis. No Factor XIIa formation could be demonstrated. The complement alternate pathway also can be activated.

8 USE IN SPECIFIC POPULATIONS

8.1 Pregnancy

Risk Summary

There are no data on ULTRAVIST Injection use in pregnant women to evaluate for a drug-associated risk of major birth defects, miscarriage, or adverse maternal or fetal outcomes. Iopromide crosses the placenta and reaches fetal tissues in small amounts (see Data). In animal reproduction studies, intravenous administration of iopromide to pregnant rats and rabbits during organogenesis at doses up to 0.35 and 0.7 times, respectively, the maximum recommended human dose based on body surface area resulted in no relevant adverse developmental effects (see Data). .

The estimated background risk of major birth defects and miscarriage for the indicated population is unknown. All pregnancies have a background risk of birth defects, loss, or other adverse outcomes. In the U.S. general population, the estimated background risk of major birth defects and miscarriage in clinically recognized pregnancies is 2 to 4% and 15 to 20%, respectively.

Data

Human Data

Limited case reports demonstrate that intravenously administered iodinated contrast agents, including iopromide, cross the placenta and are visualized in the digestive tract of exposed infants after birth.

Animal Data

Reproduction studies performed with intravenous iopromide in rats (day 6 to 15 of gestation) and rabbits (day 6 to 18 of gestation) at doses up to dose levels of 0, 0.37, 1.11 and 3.7 g I/iodine per kg (2.2 times the maximum recommended dose for a 50 kg human, or approximately 0.7corresponding to doses up to 0.35 times the(rats) and 0.7 times (rabbits) the maximum human recommended dose following normalization of the data tobased on body surface area estimates) have revealed no evidence of direct harm to the fetus. Embryolethality. Iopromide was not teratogenic at any dose level in rats and rabbits and embryolethality was observed in rabbits that received 3.7 g I/iodine per kg, but this was considered to have been secondary to maternal toxicity.

8.2 Lactation

Risk Summary

There are no data on the presence of iopromide in human milk, the effects on the breastfed infant, or the effects on milk production. Iodinated contrast agents are poorly excreted into human milk and are poorly absorbed by the gastrointestinal tract of a breastfed infant. The developmental and health benefits of breastfeeding should be considered along with the mother’s clinical need for ULTRAVIST Injection and any potential adverse effects on the breastfed infant from ULTRAVIST Injection or from the underlying maternal condition (see Clinical Considerations).

Clinical Considerations

Interruption of breastfeeding after exposure to iodinated contrast agents is not necessary because the potential exposure of the breastfed infant to iodine is small. However, a lactating woman may consider interrupting breastfeeding and pumping and discarding breast milk for 12 to 24 hours (approximately 5 elimination half-lives) after ULTRAVIST Injection administration in order to minimize drug exposure to a breast fed infant.

8.4 Pediatric Use

The safety and efficacy of ULTRAVIST injection 300 mg iodine per mL have been established in pediatric patients over 2 years of age for CT of the body and head. Use of ULTRAVIST injection in these age groups is supported by evidence from adequate and well controlled studies of ULTRAVIST injection in adults and additional safety data obtained in literature and other reports in a total of 274 pediatric patients. Of these, there were 131 children (2–12 years), 57 adolescents, and 86 children of unreported or other ages. There were 148 females, 94 males and 32 in whom gender was not reported. The racial distribution was: Caucasian 93 (33.9%), Black 1 (0.4%), Asian 6 (2.2%), and unknown 174 (63.5%). Eighty-seven of these patients were evaluated in intravenous contrast computerized tomography (CT) (n=87).

In these pediatric patients, a concentration of 300 mg iodine per mL was employed for intravenous contrast CT. Most pediatric patients received initial volumes of 1–2 mL/kg.

Optimal doses of ULTRAVIST injection have not been established because different injection volumes, concentrations and injection rates were not studied. The relationship of the volume of injection with respect to the size of the target vascular bed has not been established. The potential need for dose adjustment on the basis of immature renal function has not been established. In the pediatric population, the pharmacokinetic parameters have not been established.

Pediatric patients at higher risk of experiencing an adverse reaction during and after administration of any contrast agent include those with asthma, a sensitivity to medication and/or allergens, cyanotic and acyanotic heart disease, congestive heart failure, or a serum creatinine greater than 1.5 mg/dL.

Thyroid function tests indicative of thyroid dysfunction, characterized by hypothyroidism or transient thyroid suppression have been reported following iodinated contrast media administration in pediatric patients, including term and preterm neonates; some patients were treated for hypothyroidism. After exposure to iodinated contrast media, individualize thyroid function monitoring in pediatric patients 0 to 3 years of age based on underlying risk factors, especially in term and preterm neonates [see Warnings and Precautions (5.6) and Adverse Reactions (6.2)].

The injection rates in small vascular beds, and the relationship of the dose by volume or concentration in small pediatric patients have not been established. Exercise caution in selecting the dose.

The safety and effectiveness of ULTRAVIST injection 300 iodine per mL have not been established in pediatric patients below the age of two for CT of the body and head . The safety and effectiveness of ULTRAVIST injection 370 mg iodine per mL have not been established in pediatric patients of any age for CT of the body and head

8.5 Geriatric Use

Middle-aged and elderly patients, without significantly impaired renal function, who received ULTRAVIST injection in doses corresponding to 9–30 g iodine, had mean steady-state volumes of distribution that ranged between 30–40 L. Mean total and renal clearances were between 81–125 mL/min and 70–115 mL/min respectively in these patients, and were similar to the values found in the young volunteers. The distribution phase half-life in this patient population was 0.1 hour, the main elimination phase half-life was 2.3 hours, and the terminal elimination phase half-life was 40 hours. The urinary excretion (97% of the dose) and fecal excretion (2%) was comparable to that observed in young healthy volunteers, suggesting that, compared to the renal route, biliary and/or gastrointestinal excretion is not significant for iopromide.

8.6 Renal Impairment

In patients with renal impairment, opacification of the calyces and pelves by iopromide may be delayed due to slower renal excretion of iopromide.

A pharmacokinetic study in patients with mild (n=2), moderate (n=6), and severe (n=3) renal impairment was conducted. The total clearance of iopromide was decreased proportionately to the baseline decrease in creatinine clearance. The plasma AUC increased about 2-fold in patients with moderate renal impairment and 6-fold in patients with severe renal impairment compared to subjects with normal renal function. The terminal half-life increased from 2.2 hrs for subjects with normal renal function to 11.6 hrs in patients with severe renal impairment. The peak plasma concentration of iopromide was not influenced by the extent of renal impairment. Exercise caution and use the lowest necessary dose of ULTRAVIST injection in patients with renal dysfunction [see Warnings and Precautions (5.2)].

10 OVERDOSAGE

The adverse effects of overdosage are life-threatening and affect mainly the pulmonary and cardiovascular systems. Treatment of an overdosage is directed toward the support of all vital functions, and prompt institution of symptomatic therapy.

Iopromide binds negligibly to plasma or serum protein and can, therefore, be dialyzed.

11 DESCRIPTION

ULTRAVIST(iopromide) injection is a nonionic, water soluble x-ray contrast agent for intravascular administration. The chemical name for iopromide is N,N'-Bis(2,3-dihydroxypropyl) –2,4,6–triiodo–5– [(methoxyacetyl)amino] –N-methyl–1,3-benzenedicarboxamide. Iopromide has a molecular weight of 791.12 (iodine content 48.12%).

Iopromide has the following structural formula:

ULTRAVIST injection is a nonionic sterile, clear, colorless to slightly yellow, odorless, pyrogen-free aqueous solution of iopromide, containing 2.42 mg/mL tromethamine buffer and 0.1 mg/mL edetate calcium disodium stabilizer.

ULTRAVIST is available as an Imaging Bulk Package in two strengths:

300 mg Iodine per mL provides 623.4 mg/mL iopromide

370 mg Iodine per mL provides 768.86 mg/mL iopromide

During the manufacture of ULTRAVIST injection, sodium hydroxide or hydrochloric acid may be added for pH adjustment. ULTRAVIST injection has a pH of 7.4 (6.5–8) at 25± 2°C, is sterilized by autoclaving and contains no preservatives.

The iodine concentrations (mg Iodine per mL) available have the following physicochemical properties:

Property |  | ULTRAVIST; INJECTION | ULTRAVIST; INJECTION
Property |  | 300 mg Iodine per mL | 370 mg Iodine per mL
Osmolality*(mOsmol/kg water) | @ 37°C | 607 | 774
Osmolarity*(mOsmol/L) | @ 37°C | 428 | 496
Viscosity (cP) | @ 20°C; @ 37°C | 9.2; 4.9 | 22; 10
Density (g/mL) | @ 20°C; @ 37°C | 1.330; 1.322 | 1.409; 1.399

*Osmolality was measured by vapor-pressure osmometry. Osmolarity was calculated from the measured osmolal concentrations.

Solutions of ULTRAVIST injection 300 mg Iodine per mL and 370 mg Iodine per mL have osmolalities respectively 2.1 and 2.7 times that of plasma (285 mOsmol/kg water).

12 CLINICAL PHARMACOLOGY

12.1 Mechanism of Action

ULTRAVIST injection is a nonionic, water soluble, tri-iodinated x-ray contrast agent for intravascular administration.

Intravascular injection of ULTRAVIST injection opacifies those vessels in the path of flow of the contrast agent, permitting radiographic visualization of the internal structures until significant hemodilution occurs.

12.2 Pharmacodynamics

Following ULTRAVIST injection administration, the degree of contrast enhancement is directly related to the iodine content in the administered dose; peak iodine plasma levels occur immediately following rapid intravenous injection. Iodine plasma levels fall rapidly within 5 to 10 minutes. This can be accounted for by the dilution in the vascular and extravascular fluid compartments.

Intravascular Contrast: Contrast enhancement appears to be greatest immediately after bolus injections (15 seconds to 120 seconds). Thus, greatest enhancement may be detected by a series of consecutive two-to-three second scans performed within 30 to 90 seconds after injection (that is, dynamic computed tomographic imaging).

ULTRAVIST injection may be visualized in the renal parenchyma within 30–60 seconds following rapid intravenous injection. Opacification of the calyces and pelves in patients with normal renal function becomes apparent within 1–3 minutes, with peak contrast occurring within 5–15 minutes.

In contrast CT, some performance characteristics are different in the brain and body. In contrast CT of the body, iodinated contrast agents diffuse rapidly from the vascular into the extravascular space. Following the administration of iodinated contrast agents, the increase in tissue density to x-rays is related to blood flow, the concentration of the contrast agent, and the extraction of the contrast agent by various interstitial tissues. Contrast enhancement is thus due to any relative differences in extravascular diffusion between adjacent tissues.

In the normal brain with an intact blood-brain barrier, contrast is generally due to the presence of iodinated contrast agent within the intravascular space. The radiographic enhancement of vascular lesions, such as arteriovenous malformations and aneurysms, depends on the iodine content of the circulating blood pool.

In tissues with a break in the blood-brain barrier, contrast agent accumulates within interstitial brain tissue. The time to maximum contrast enhancement can vary from the time that peak blood iodine levels are reached to 1 hour after intravenous bolus administration. This delay suggests that radiographic contrast enhancement is at least in part dependent on the accumulation of iodine containing medium within the lesion and outside the blood pool. The mechanism by which this occurs is not clear.

For information on coagulation parameters, fibrinolysis and complement system [see Drug Interactions (7.2)].

12.3 Pharmacokinetics

Distribution

After intravenous administration to healthy young volunteers, plasma iopromide concentration time profile shows an initial distribution phase with a half-life of 0.24 hour; a main elimination phase with a half-life of 2 hours; and a terminal elimination phase with a half-life of 6.2 hours. The total volume of distribution at steady state is about 16 L suggesting distribution into extracellular space. Plasma protein binding of iopromide is 1%.

Iodinated contrast agents may cross the blood-brain barrier [see Warnings and Precautions (5.8)].

Metabolism

Iopromide is not metabolized.

Elimination

The amounts excreted unchanged in urine represent 97% of the dose in young healthy subjects. Only 2% of the dose is recovered in the feces. Similar recoveries in urine and feces are observed in middle-aged and elderly patients. This finding suggests that, compared to the renal route, biliary and/or gastrointestinal excretion is not important for iopromide. During the slower terminal phase, only 3% of the dose is eliminated; 97% of the dose is disposed of during the earlier phases, the largest part of which occurs during the main elimination phase. The ratio of the renal clearance of iopromide to the creatinine clearance is 0.82 suggesting that iopromide is mainly excreted by glomerular filtration. Additional tubular reabsorption is possible. Pharmacokinetics of iopromide at intravenous doses up to 80 g iodine, are dose proportionate and first order.

The mean total and renal clearances are 107 mL/min and 104 mL/min, respectively.

Specific Populations

A pharmacokinetic study was conducted in 11 patients with renal impairment [see Use in Specific Populations (8.6)].

13 NONCLINICAL TOXICOLOGY

13.1 Carcinogenesis, Mutagenesis, Impairment of Fertility

Long-term animal studies have not been performed with iopromide to evaluate carcinogenic potential or effects on fertility. Iopromide was not genotoxic in a series of studies including the Ames test, an in vitro human lymphocytes analysis of chromosomal aberrations, an in vivo mouse micro-nucleus assay, and in an in vivo mouse dominant lethal assay.

14 CLINICAL STUDIES

ULTRAVIST injection was administered to 708 patients; 1 patient was less than 18 years of age, 347 patients were between 18 and 59 years of age, and 360 patients were equal to or greater than 60 years of age; the mean age was 56.6 years (range 17–88). Of the 708 patients, 446 (63%) were male and 262 (37%) were female. The racial distribution was: Caucasian 463 (65.4%), Black 95 (13.4%), Hispanic 36 (5.1%), Asian 11 (1.6 %), and other or unknown 103 (14.5%). Efficacy assessment was based on the global evaluation of the quality of the radiographs by rating visualization as either excellent, good, poor, or no image, and on the ability to make a diagnosis. Contrast CT of head and body was evaluated in three randomized, double-blind clinical trials of ULTRAVIST injection, 300 mg Iodine per mL, in 95 patients with vascular disorders. Visualization ratings were good or excellent in 99% of the patients; a radiologic diagnosis was made in the majority of the patients. A confirmation of contrast CT findings by other diagnostic methods was not obtained.

ULTRAVIST injection was evaluated in a blinded reader trial for CT of the head and body. Among the 382 patients who were evaluated with ULTRAVIST injection 370 mg Iodine per mL, visualization ratings were good or excellent in approximately 97% of patients.

16 HOW SUPPLIED/STORAGE AND HANDLING

ULTRAVIST injection is a sterile, clear, colorless to slightly yellow, odorless, pyrogen-free aqueous solution available in two strengths.

ULTRAVIST injection 300 mg Iodine per mL Imaging Bulk Package (Multiple-Dose container)

200 mL fill/250 mL bottles (carton of 10) NDC 50419-344-23

500 mL fill/500 mL bottles (carton of 8) NDC 50419-344-65

ULTRAVIST injection 370 mg Iodine per mL Imaging Bulk Package (Multiple-Dose container)

200 mL fill/250 mL bottles (carton of 10) NDC 50419-346-28

500 mL fill/500 mL bottles (carton of 8) NDC 50419-346-65

STORAGE

Store ULTRAVIST injection Imaging Bulk Package at 25°C (77°F); excursions permitted to 15–30°C (59–86°F) and protected from light [see USP Controlled Room Temperature].

17 PATIENT COUNSELING INFORMATION

Instruct patients receiving ULTRAVIST injection to inform their physician or healthcare provider of the following:

- Advise patients to inform their physician if they develop a rash after receiving ULTRAVIST [see Warnings and Precautions (5.9)]
- Lactation: Advise lactating women that interruption of breast feeding is not necessary, however, a lactating woman may consider interrupting breastfeeding and pumping and discarding breast milk for 12 to 24 hours after ULTRAVIST Injection administration to minimize exposure to the breastfed infant (8.2)
- Thyroid Dysfunction – Advise parents/caregivers about the risk of developing thyroid dysfunction after ULTRAVIST administration. Advise parents/caregivers about when to seek medical care for their child to monitor thyroid function [see Warnings and Precautions (5.6)].
Manufactured for:
  Bayer HealthCare Pharmaceuticals Inc.
  Whippany, NJ 07981

© 2018, Bayer HealthCare Pharmaceuticals Inc. All rights reserved.

Package/Label Principal Display Panel

NDC 50419-344-65 8 x 500 mL

sterile solution

imaging bulk package

not for direct infusion

Ultravist®

(brand of iopromide)

300 mg Iodine per mL

injection

Rx only

Package/Label Principal Display Panel

NDC 50419-346-65 8 x 500 mL

sterile solution

imaging bulk package

not for direct infusion

Ultravist®

(brand of iopromide)

370 mg Iodine per mL

injection

Rx only